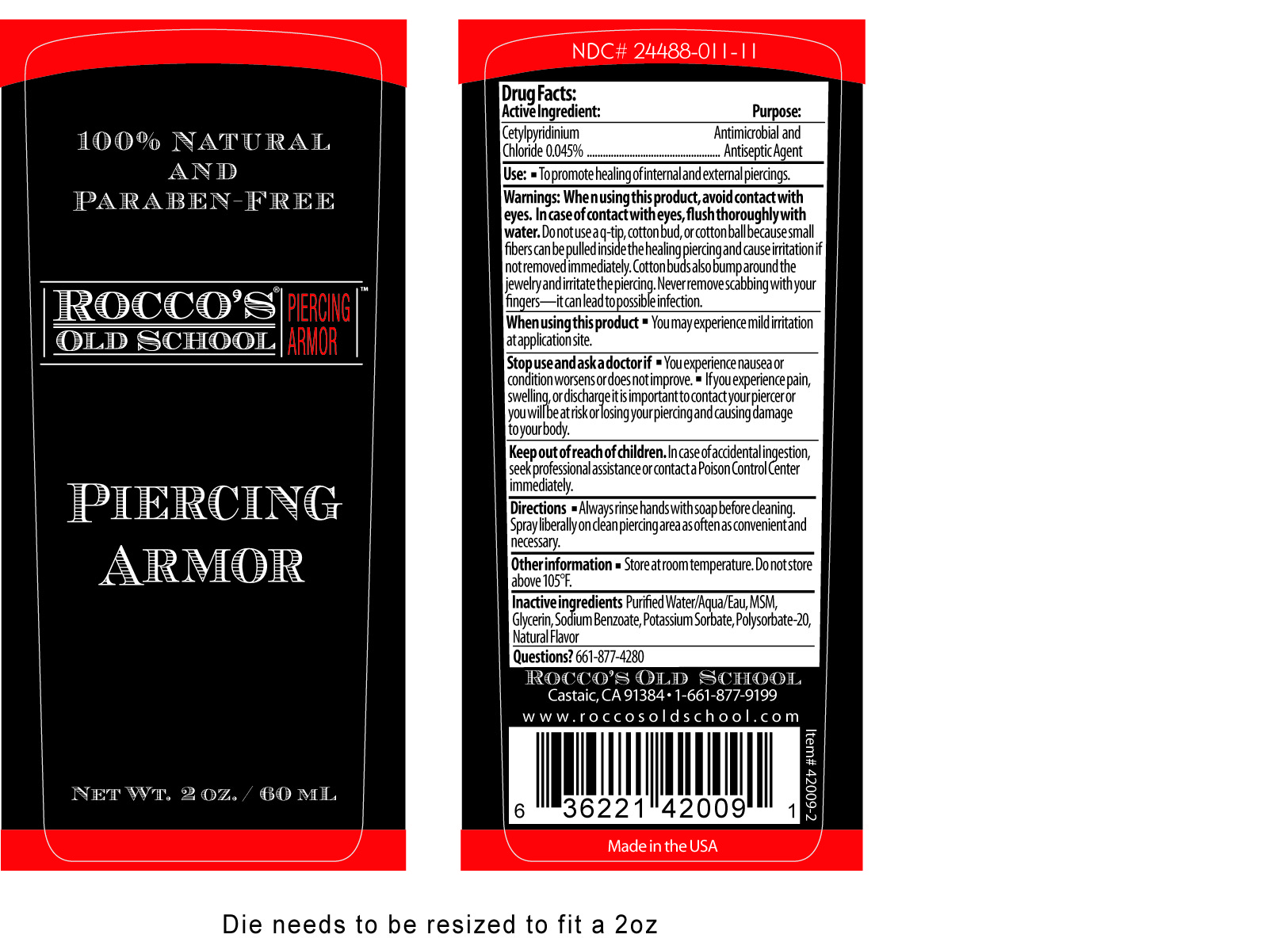 DRUG LABEL: Roccos Old School
NDC: 24488-011 | Form: SPRAY
Manufacturer: Rocco's Old School
Category: otc | Type: HUMAN OTC DRUG LABEL
Date: 20110301

ACTIVE INGREDIENTS: CETYLPYRIDINIUM CHLORIDE  .027 mL/60 mL
INACTIVE INGREDIENTS: WATER ; DIMETHYL SULFONE; GLYCERIN; SODIUM BENZOATE; POTASSIUM SORBATE; POLYSORBATE 20

Drug Facts

Active Ingredient: Purpose

Cetylpyridinium Chloride 0.045% ................................................Antimicrobial and Antiseptic Agent

Use:

- To promote healing of internal and external piercings.

Warnings:

When using this product, avoid contact with eyes. In case of contact with eyes, flush thoroughly with water. Do not use a q-tip, cotton bud, or cotton ball because small fibers can be pulled inside the healing piercing and cause irritation if not removed immediately. Cotton buds also bump around the jewelry and irritate the piercing. Never remove scabbing with your fingers--it can lead to possible infection.

When using this product

- You may experience mild irritation at application site.

Stop use and ask a doctor if

- You experience nausea or condition worsens or does not improve.
- If you experience pain, swelling or discharge it is important to contact your piercer or you will be at risk of losing your piercing and causing damage to your body.

Keep out of reach of children.

In case of accidental ingestion, seek professional assistance or contact a Poison Control Center immediately.

Directions

- Always rinse hands with soap before cleaning.
- Spray liberally on clean piercing area as often as convenient and necessary.

Other information

- Store at room temperature. Do not store above 105°F.

Inactive ingredients

Purified Water/Aqua/Eau, MSM, Glycerin, Sodium Benzoate, potassium Sorbate, Polysorbate-20, Natural Flavor

Questions?

661-877-4280

PACKAGE LABEL

Placeholder Text